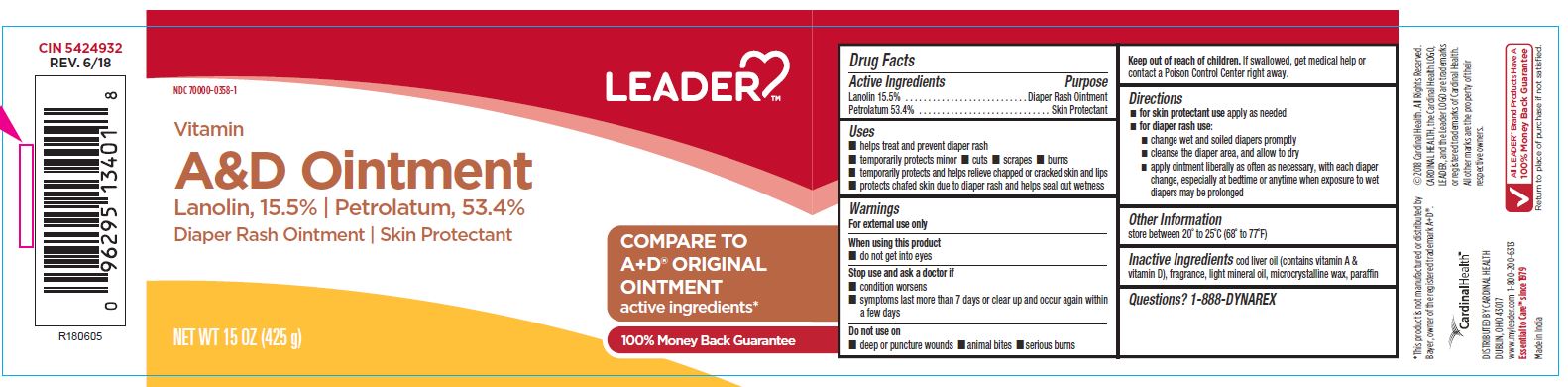 DRUG LABEL: LDR Vitamans A and D
NDC: 70000-0358 | Form: OINTMENT
Manufacturer: Cardinal Health
Category: otc | Type: HUMAN OTC DRUG LABEL
Date: 20251125

ACTIVE INGREDIENTS: PETROLATUM 53.4 g/100 g; LANOLIN 15.5 g/100 g
INACTIVE INGREDIENTS: LAVENDER OIL; MICROCRYSTALLINE WAX; LIGHT MINERAL OIL; COD LIVER OIL

CR-1157 A&D Ointment

Active Ingredients

- Lanolin 15.5%
- Petrolatum 53.4%

Purpose

Diaper Rash Ointment

Skin Protectant

Uses

- Helps treat and prevent diaper rash
- temporarily protects minor cuts, scrapes, burns
- temporarily protects and helps relieve chapped or cracked skin and lips
- protects chafed skin due to diaper rash and helps seal out wetness

Warnings

For external use only

When using this product

do not get into eyes

Stop use and ask a doctor if

- conditions worsen
- symptoms last more than 7 days or clear up and occur again within a few days

Do not use on

- deep or puncture wounds
- animal bites
- serious burns

KEEP OUT OF REACH OF CHILDREN

If swallowed, get medical help or contact a Poison Control Center right away.

Directions

- for skin protectant use apply as needed
- for diaper rash use:
  - change wet and soiled diapers promptly
  - cleanse the diaper area, and allow to dry
  - apply ointment liberally as often as necessary, with each diaper change, especially at bedtime or anytime when exposure to wet diapers may be prolonged

Other Information

store between 20° to 25°C, 68° to 77°F

Inactive Ingredients

cod liver oil; contains vitamin A & vitamin D, fragrance, light mineral oil, microcrystalline wax, paraffin

Questions

1-888-DYNAREX